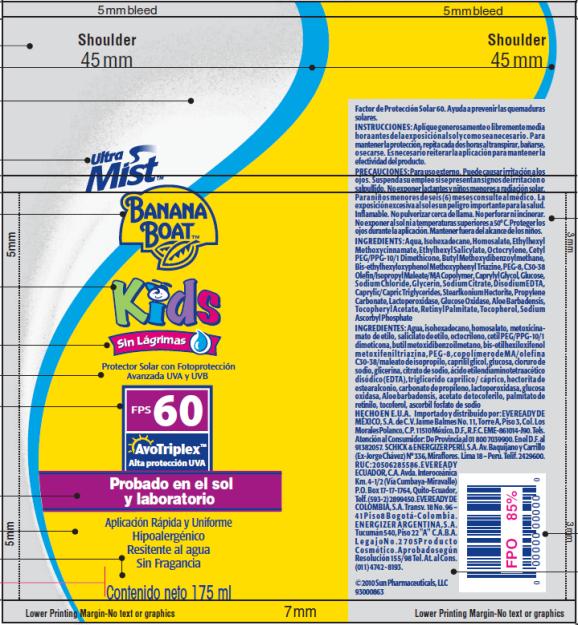 DRUG LABEL: Banana Boat Ultra Mist Kids FPS 60 LATAM
NDC: 17630-2045 | Form: SPRAY
Manufacturer: Accra-Pac, Inc.
Category: otc | Type: HUMAN OTC DRUG LABEL
Date: 20100424

ACTIVE INGREDIENTS: HOMOSALATE 0.10 mL/1 mL; OCTINOXATE 0.075 mL/1 mL; OCTISALATE 0.05 mL/1 mL; OCTOCRYLENE 0.05 mL/1 mL; AVOBENZONE 0.03 mL/1 mL
INACTIVE INGREDIENTS: BEMOTRIZINOL; CAPRYLYL GLYCOL; SODIUM CHLORIDE; GLYCERIN; SODIUM CITRATE; EDETATE DISODIUM; MEDIUM-CHAIN TRIGLYCERIDES; PROPYLENE CARBONATE; GLUCOSE OXIDASE; ALOE VERA LEAF; .ALPHA.-TOCOPHEROL ACETATE, D-; VITAMIN A PALMITATE; SODIUM ASCORBYL PHOSPHATE; POLYETHYLENE GLYCOL 400

Banana Boat Ultra Mist Kids FPS 60 LATAM

Drug Facts

Active Ingredients

Homosalate 0.10mL / 1mL

Octinoxate 0.075mL / 1mL

Octisalate 0.05mL / 1mL

Octocrylene 0.05mL / 1mL

Avobenzone 0.03mL / 1mL

INSTRUCCIONES:

Aplíque generosamente o libremente media hora antes de la exposición al sol y como sea necesario. Para mantener la protección, repita cada dos horas al transpirar, bañarse, o secarse. Es necesario reiterar la aplicación para mantener la efectividad del producto.

PRECAUCIONES:

Para uso externo. Puede causar irritación a los ojos. Suspenda su empleo si se presentan signos de irritación o salpullido. No exponer lactantes y niños menores a radiación solar. Para niños menores de seis (6) meses consulte al médico. La exposición excesiva al sol es un peligro importante para la salud. Inflamable. No pulverizar cerca de llama. No perforar ni incinerar. No exponer al sol ni a temperaturas superiores a 50° C. Proteger los ojos durante la aplicación. Mantener fuera del alcance de los niños.

INGREDIENTS:

Aqua, Isohexadecane, Homosalate, Ethylhexyl Methoxycinnamate, Ethylhexyl Salicylate, Octocrylene, Cetyl PEG/PPG-10/1 Dimethicone, Butyl Methoxydibenzoylmethane, Bis-ethylhexyloxyphenol Methoxyphenyl Triazine, PEG-8, C30-38 Olefin/Isopropyl Maleate/MA Copolymer, Caprylyl Glycol, Glucose, Sodium Chloride, Glycerin, Sodium Citrate, Disodium EDTA, Caprylic/Capric Triglycerides, Stearlkonium Hectorite, Propylene Carbonate, Lactoperoxidase, Glucose Oxidase, Aloe Barbadensis, Tocopheryl Acetate, Retinyl Palmitate, Tocopherol, Sodium Ascorbyl Phosphate

INGREDIENTES:

Agua, isohexadecano, homosalato, metoxicinamato de etilo, salicilato de etilo, octocrileno, cetil PEG/PPG-10/1 dimeticona, butil metoxidibenzoilmetano, bis-etilhexiloxifenol metoxifenil triazina, PEG-8, copolímero de MA/olefin C30-38/maleato de isopropilo, caprilil glicol, glucosa, cloruro de sodio, glicerina, citrato de sodio, ácido etilendiaminotetraacético disódico (EDTA), triglicerido caprilico / cáprico, hectorita de estearalconio, carbonato de propileno, lactoperoxidasa, glucose oxidasa, Aloe barbadensis, acetato de tocoferilo, palmitato de retinilo, tocoferol, ascorbil fosfato de sodio

HECHO EN E.U.A.

Importado y distribuido por: EVEREADY DE MÉXICO, S.A. de C.V. Jaime Balmes No. 11, Torre A, Piso 3, Col. Los Morales Polanco, C.P. 11510 México, D.F., R.F.C. EME-861014-J90. Tels. Atención al Consumidor: De Provincia al 01 800 7039900. En el D.F. al 91382057. SCHICK & ENERGIZER PERÚ, S.A. Av. Baquíjano y Carrillo (Ex-Jorge Chávez) N° 336, Miraflores. Lima 18 – Perú. Telif. 2429600. RUC: 20506285586. EVEREADY ECUADOR, C.A. Avda. Interoceánica Km. 4-1/2 (Vía Cumbaya-Miravalle) P.O. Box 17-17-1764, Quito-Ecuador, Telf. (593-2) 2899450. EVEREADY DE COLOMBIA, S.A. Transv. 18 No. 96 – 41 P i s o 8 B o g o t á - C o l omb i a . ENERGIZER ARGENTINA, S.A. Tucumán 540, Piso 22 "A" C.A.B.A. L e g a j o N o . 2 7 0 5 P r o d u c t o Cosmé t i co. Aprobado s e gún Resolución 155/98 Tel. At. al Cons. (011) 4742 - 8193.

©2010 Sun Pharmaceuticals, LLC

Manufactured by: Accra Pac, Inc (dba KIK Custom Products)

PRINCIPAL DISPLAY PANEL

Ultra
Mist TM
BANANA
BOATTM
Kids
Sin Lágrimas
Protector Solar con Fotoprotección
Avanzada UVA y UVB
FPS 60
AvoTriplex TM
Alta protección UVA
Probado en el sol
y laboratorio
Aplicación Rápida y Uniforme
Hipoalergénico
Resitente al agua
Sin Fragancia
Contenido neto 175 ml